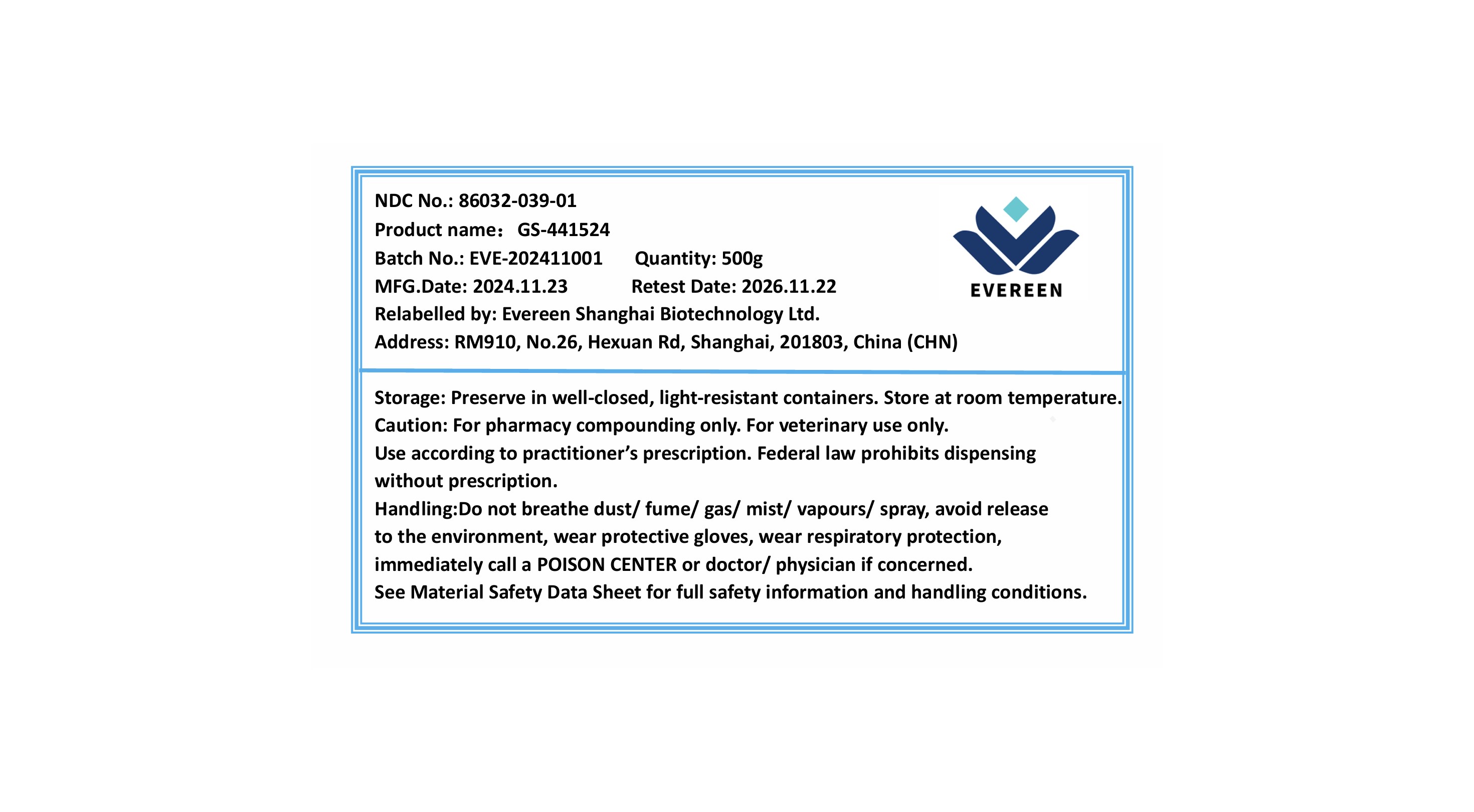 DRUG LABEL: GS-441524
NDC: 86032-039 | Form: POWDER
Manufacturer: Evereen Shanghai Biotechnology Ltd.
Category: other | Type: BULK INGREDIENT - ANIMAL DRUG
Date: 20250121

ACTIVE INGREDIENTS: GS-441524 1 g/1 g

GS-441524